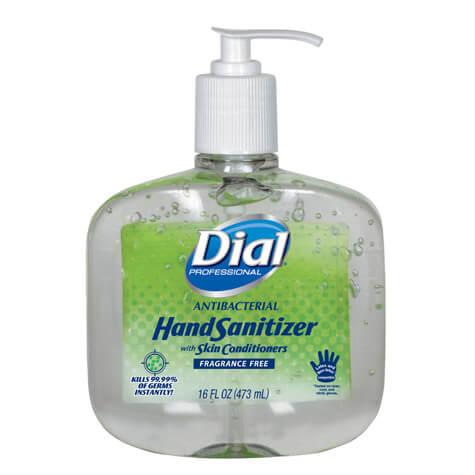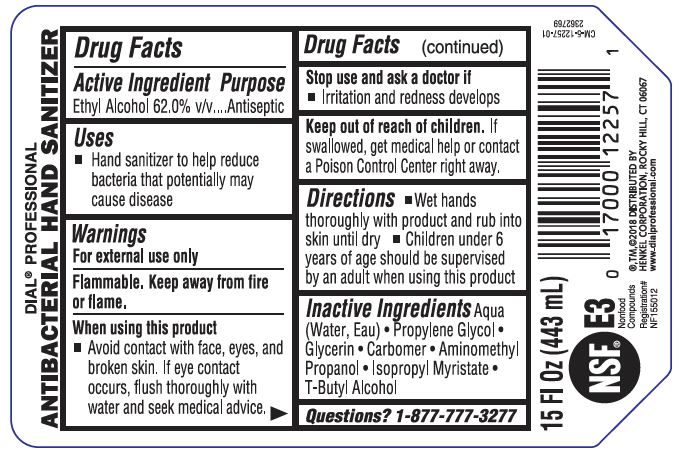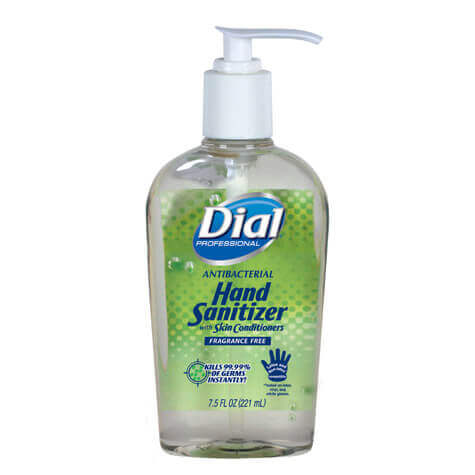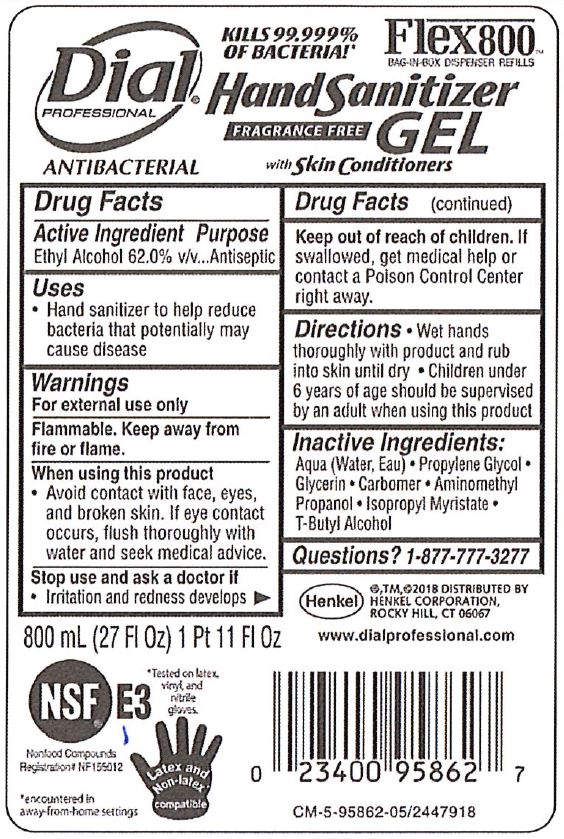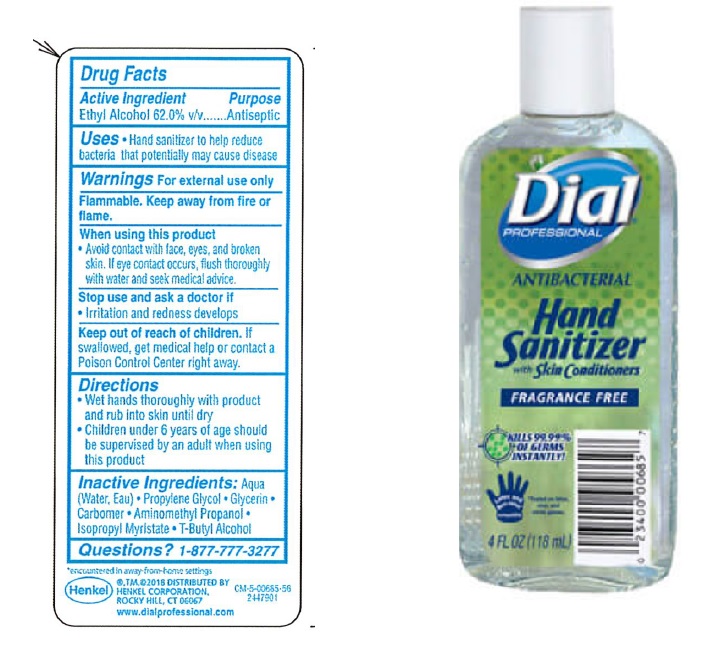 DRUG LABEL: Hand Sanitizer-Gel
NDC: 50663-003 | Form: GEL
Manufacturer: Zotos International Inc
Category: otc | Type: HUMAN OTC DRUG LABEL
Date: 20200427

ACTIVE INGREDIENTS: ALCOHOL 60.146532 mL/100 mL
INACTIVE INGREDIENTS: GLYCERIN 0.4985 mL/100 mL; WATER 38.191 mL/100 mL; Propylene Glycol 0.5 mL/100 mL; AMINOMETHYLPROPANOL 0.14725 mL/100 mL; CARBOMER HOMOPOLYMER, UNSPECIFIED TYPE 0.297 mL/100 mL; ISOPROPYL MYRISTATE 0.147 mL/100 mL; TERT-BUTYL ALCOHOL 0.072264 mL/100 mL

Active Ingredient(s)

Ethyl Alcohol 62% v/v. Purpose: Antiseptic

Purpose

Antiseptic, Hand Sanitizer

Use

Hand Sanitizer to help reduce bacteria that potentially can cause disease.

Warnings

For external use only. Flammable. Keep away from fire or flame

When using this product keep avoid contact with face, eyes, and broken skin. if eye contact occurs, flush thoroughly with water and seek medical advice.
Stop use and ask a doctor if irritation or redness develops.
Keep out of reach of children. If swallowed, get medical help or contact a Poison Control Center right away.

Keep out of reach of children. If swallowed, get medical help or contact a Poison Control Center right away.

Directions

Wet hands thoroughly with product and rub into skin until dry.

Children under 6 years of age should be supervised by an adult when using this product.

Inactive ingredients

Aqua (Water, Eau)• Propylene Glycol• Glycerin• Carbomer • Aminomethyl Propane! • lsopropyl Myrlstate • T-Butyl Alcohol

Questions

? 1-877-777-3277

Legal entity

®,TM,©2018 Distributed by
Henkel Corporation,
Rocky Hill, CT 06067
www.dialprofessional.com